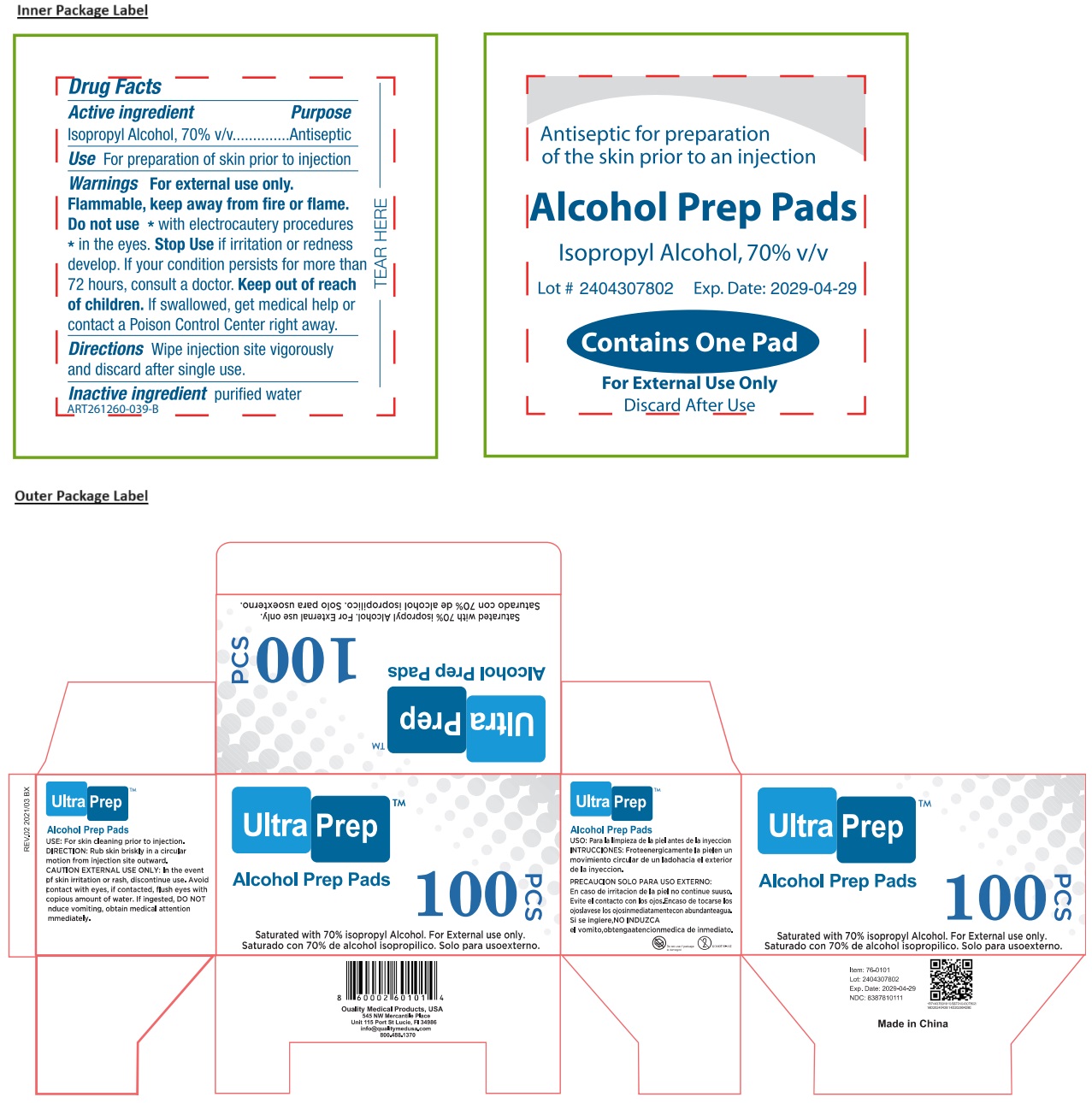 DRUG LABEL: Ultra Prep Alcohol Prep Pads
NDC: 83878-101 | Form: CLOTH
Manufacturer: Quality Medical Products USA, Inc.
Category: otc | Type: HUMAN OTC DRUG LABEL
Date: 20240716

ACTIVE INGREDIENTS: ISOPROPYL ALCOHOL 70 mL/100 mL
INACTIVE INGREDIENTS: WATER

Ultra Prep™ Alcohol Prep Pads

Active ingredient

Isopropyl Alcohol, 70% v/v

Purpose

Antiseptic

Use

For preparation of skin prior to injection

Warnings

For external use only.

Flammable, keep away from fire or flame.

Do not use * with electrocautery procedures * in the eyes. Stop Use if irritation or redness develop. If your condition persists for more than 72 hours, consult a doctor.

Keep out of reach of children. If swallowed, get medical help or contact a Poison Control Center right away.

Directions

Wipe injection site vigorously and discard after single use.

Inactive ingredient

purified water

Saturated with 70% isopropyl Alcohol.

USE: For skin cleaning prior to injection.

DIRECTION: Rub skin briskly in a circular motion from injection site outward.

CAUTION EXTERNAL USE ONLY: In the event of skin irritation or rash, discontinue use. Avoid contact with eyes, if contacted, flush eyes with copious amount of water. If ingested, DO NOT induce vomiting, obtain medical attention immediately.

Quality Medical Products, USA
545 NW Mercantile Place
Unit 115 Port St Lucie, Fl 34986
info@qualitymedusa.com
800.488.1370

Made in China